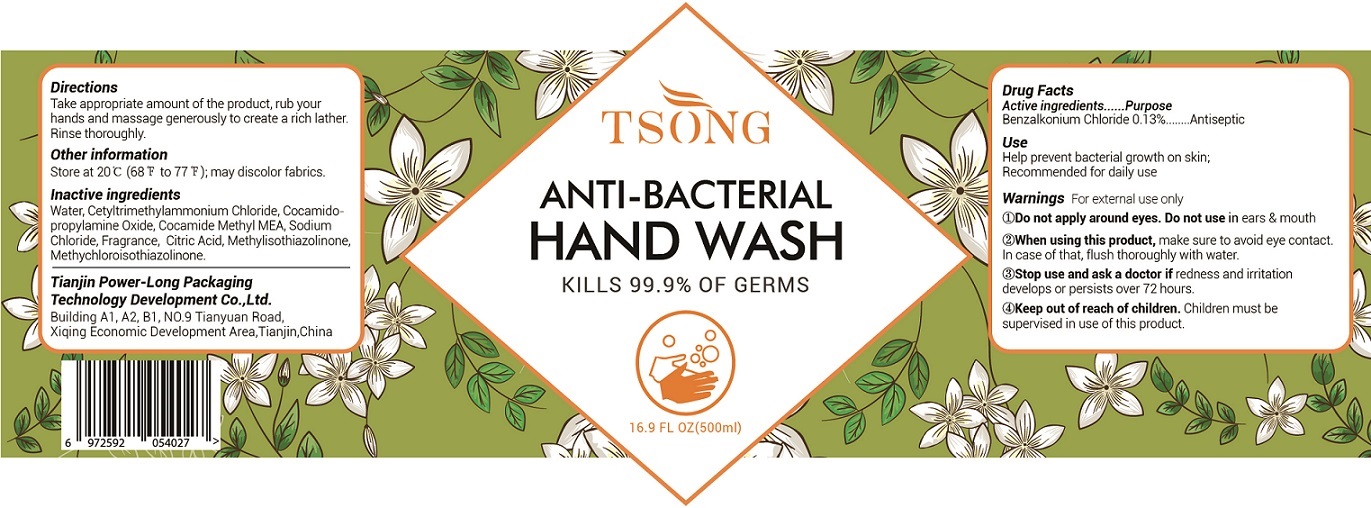 DRUG LABEL: TSONG Anti Bacterial Hand Wash
NDC: 79035-003 | Form: LIQUID
Manufacturer: Tianjin Power-Long Packaging Technology Development Co.,Ltd.
Category: otc | Type: HUMAN OTC DRUG LABEL
Date: 20231023

ACTIVE INGREDIENTS: BENZALKONIUM CHLORIDE 1.3 mg/1 mL
INACTIVE INGREDIENTS: WATER; CETRIMONIUM CHLORIDE; COCAMIDOPROPYLAMINE OXIDE; COCOYL METHYL MONOETHANOLAMINE; SODIUM CHLORIDE; CITRIC ACID MONOHYDRATE; METHYLISOTHIAZOLINONE; METHYLCHLOROISOTHIAZOLINONE

TSONG Anti-Bacterial Hand Wash

Active Ingredients

Benzalkonium Chloride 0.13%

Purpose

Antiseptic

Use

Help prevent bacterial growth on skin; Recommended for daily use.

Warnings

For external use only

Do not apply around eyes.

Do not use

in ears & mouth

When using this product,

make sure to avoid contact with eyes. In case of contact, flush thoroghly with water.

Stop use and ask a doctor if

redness or irritation develop and persist for more than 72 hours.

Keep out of reach of children.

Children must be supervised in use of this product.

Directions

Take appropriate amount of the product, rub your hands and massage generously to create a rich lather; Rinse thoroughly.

Other information

Store at 20°C (68°F to 77°F), may discolor fabrics.

Inactive ingredients

Water, Cetyltrimethylammonium Chloride, Cocoamidopropylamine Oxide, Cocamide Methyl MEA, Sodium Chloride, Fragrance, Citric Acid, Methylisothiazolinone, Methylchloroisothiazolinone.